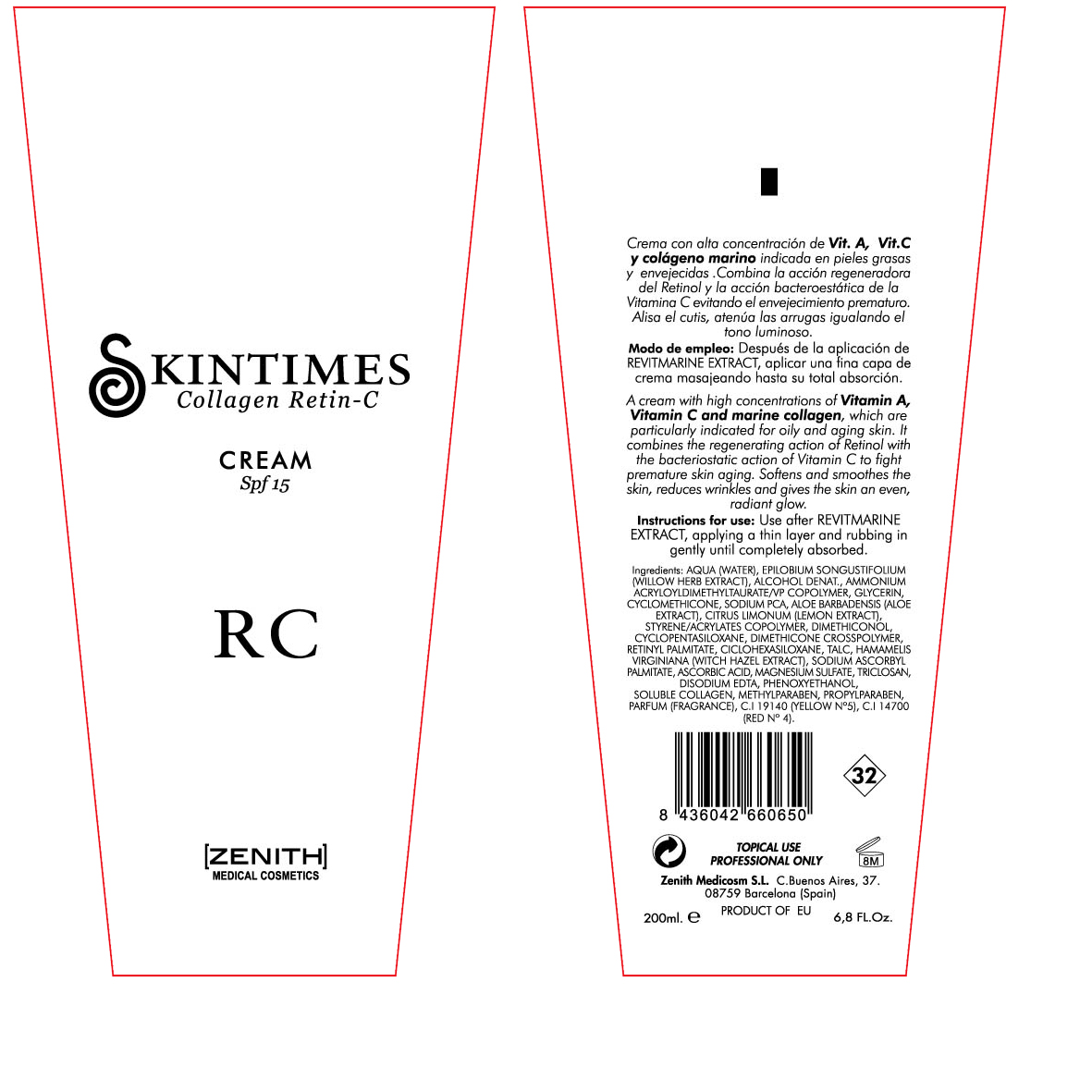 DRUG LABEL: Retin
NDC: 42248-114 | Form: CREAM
Manufacturer: Zenith Medicosm SL
Category: otc | Type: HUMAN OTC DRUG LABEL
Date: 20120121

ACTIVE INGREDIENTS: OCTINOXATE 15 mL/200 mL
INACTIVE INGREDIENTS: ALCOHOL; PROPYLPARABEN; GLYCERIN; CYCLOMETHICONE; SODIUM PYRROLIDONE CARBOXYLATE; ALOE; WATER; EPILOBIUM ANGUSTIFOLIUM LEAF; LEMON JUICE; BUTYL ESTER OF METHYL VINYL ETHER-MALEIC ANHYDRIDE COPOLYMER (125 KD); CYCLOMETHICONE 6; TALC; HAMAMELIS VIRGINIANA LEAF; SODIUM ASCORBATE; ASCORBIC ACID; MAGNESIUM SULFATE; METHYLPARABEN; COLLAGEN, SOLUBLE, FISH SKIN; AMMONIUM ACRYLOYLDIMETHYLTAURATE/VP COPOLYMER; TRICLOSAN; EDETATE DISODIUM; DIMETHICONOL (41 MPA.S); PHENOXYETHANOL; CYCLOMETHICONE 5; FD&C RED NO. 4; FD&C YELLOW NO. 5

Drug Facts

Active Ingredient

Octinoxate 7.5%

Description

A cream with high concentrations of Vitamin A, Vitamin C and marine collagen, which are particularly indicated for oily and aging skin. It combines the regenerating action of Retinol and the bateriostatic action of Vitamin C to fight premature skin aging. Softens and smoothes the skin, reduces wrinkles and gives the skin an even, radiant glow.

200ml. 6.8Fl.Oz.

Warning

TOPICAL USE

PROFESSIONAL ONLY

INDICATIONS AND USAGE

Use after REVITMARINE EXTRACT, applying a thin layer and rubbing in gently until completely absorbed.